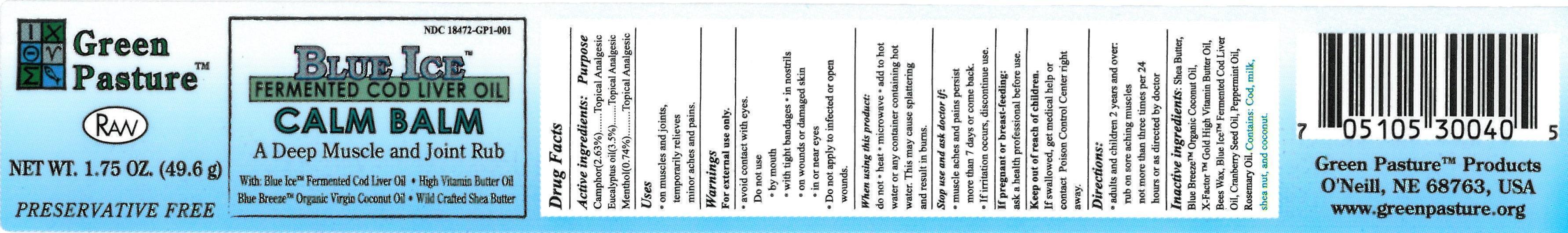 DRUG LABEL: Blue Ice Fermented Cod Liver Oil Calm Balm
NDC: 18472-175 | Form: Salve
Manufacturer: ABS Corporation
Category: otc | Type: HUMAN OTC DRUG LABEL
Date: 20140204

ACTIVE INGREDIENTS: CAMPHOR (NATURAL) 1.30 g/49.5 g; EUCALYPTUS OIL 1.73 g/49.5 g; MENTHOL 0.37 g/49.5 g
INACTIVE INGREDIENTS: SHEA BUTTER 15.59 g/49.5 g; COCONUT OIL 12.87 g/49.5 g; OLEIC ACID 7.43 g/49.5 g; WHITE WAX 5.45 g/49.5 g; COD LIVER OIL 3.86 g/49.5 g; CRANBERRY SEED OIL 10.59 g/49.5 g; PEPPERMINT OIL 0.13 g/49.5 g; ROSEMARY OIL 0.01 g/49.5 g

Blue Ice Fermented Cod Liver Oil Calm Balm

ACTIVE INGREDIENTS:

Active Ingredients |  | Purpose
Camphor (2.63%) |  | Topical Analgesic
Eucalyptus Oil (3.5%) |  | Topical Analgesic
Menthol (0.74%) |  | Topical Analgesic

PURPOSE:

Active Ingredients |  | Purpose
Camphor (2.63%) |  | Topical Analgesic
Eucalyptus Oil (3.5%) |  | Topical Analgesic
Menthol (0.74%) |  | Topical Analgesic

Keep Out of Reach of Children.

If swallowed, get medical help or contact Poison Control Center right away.

Uses:

- on muscles and joints
- temporarily relieves minor aches and pains

Warnings:

For external use only

- avoid contact with eyes.

DO NOT USE

- by mouth
- with tight bandages
- in nostrils
- on wounds or damaged skin
- in or near eyes
- Do not apply to infected or open wounds.

When using this product:

DO NOT

- heat
- microwave
- add to hot water or any container containing hot water. This may cause splattering and result in burns.

Stop Use and Ask Doctor if:

- muscle aches and pains persist more than 7 days or come back
- if irritation occurs, discontinue use

If pregnant or breast-feeding:

ask a health professional before use.

Directions:

Adults and chldren 2 years and over:

- rub on sore aching muscles
- not more than three times per 24 hours or as directed by doctor

INACTIVE INGREDIENTS:

Shea Butter, Blue Breeze Organic Coconut Oil,

X-Factor Gold High Vitamin Butter Oil, White Bees Wax,

Blue Ice Fermented Cod Liver Oil, Cranberry Seed Oil,

Peppermint Oil, Rosemary Oil.

Contains: Cod, milk, shea nut, and coconut.

PACKAGE LABEL

NDC 18472-175-01

BLUE ICE™

FERMENTED COD LIVER OIL

CALM BALM

A Deep Muscle and Joint Rub

With:

Blue Ice™ Fermented Cod Liver Oil - High Vitamin Butter Oil

Blue Breeze™ Organic Virgin Coconut Oil - Wild Crafted Shea Butter